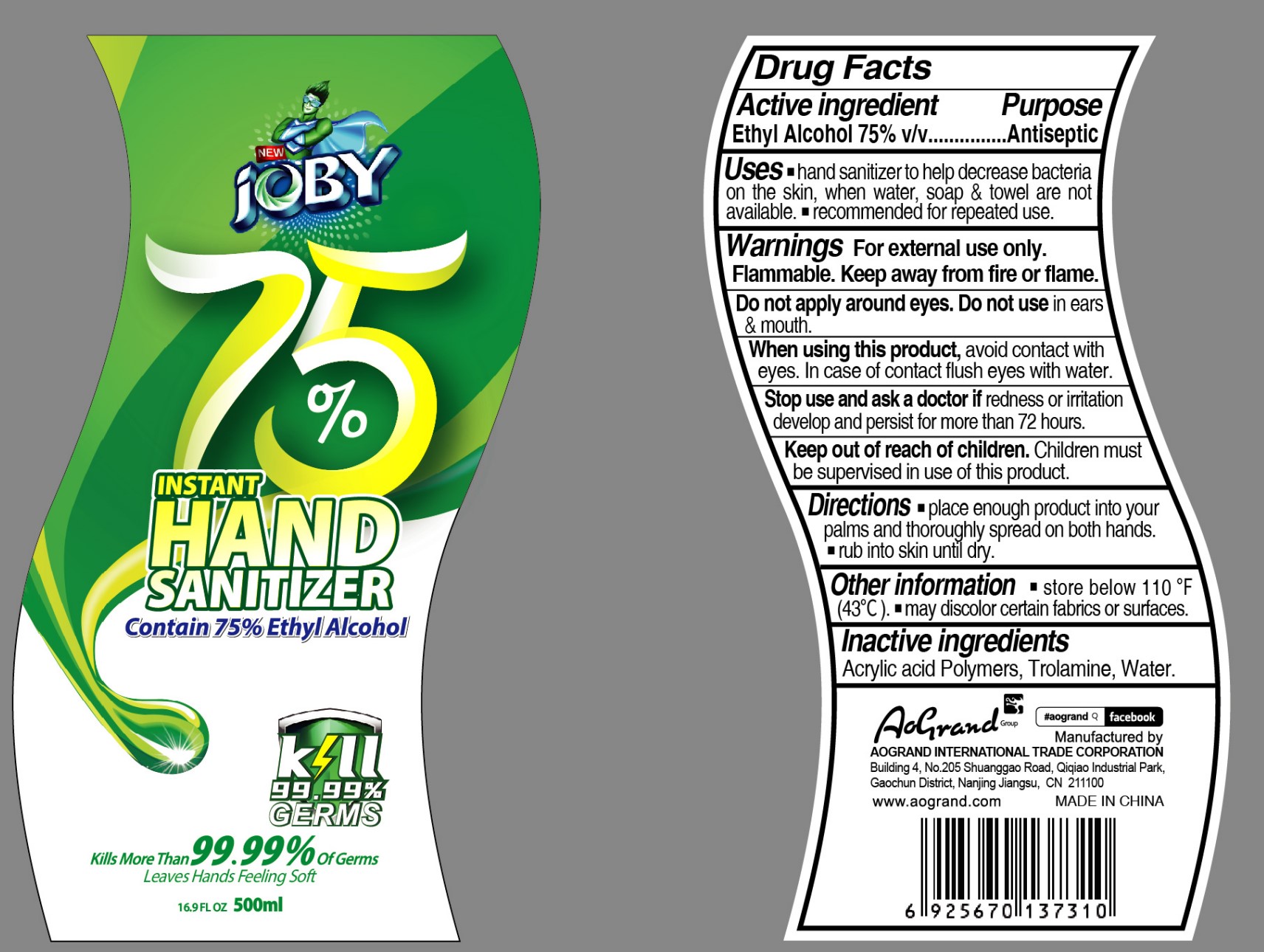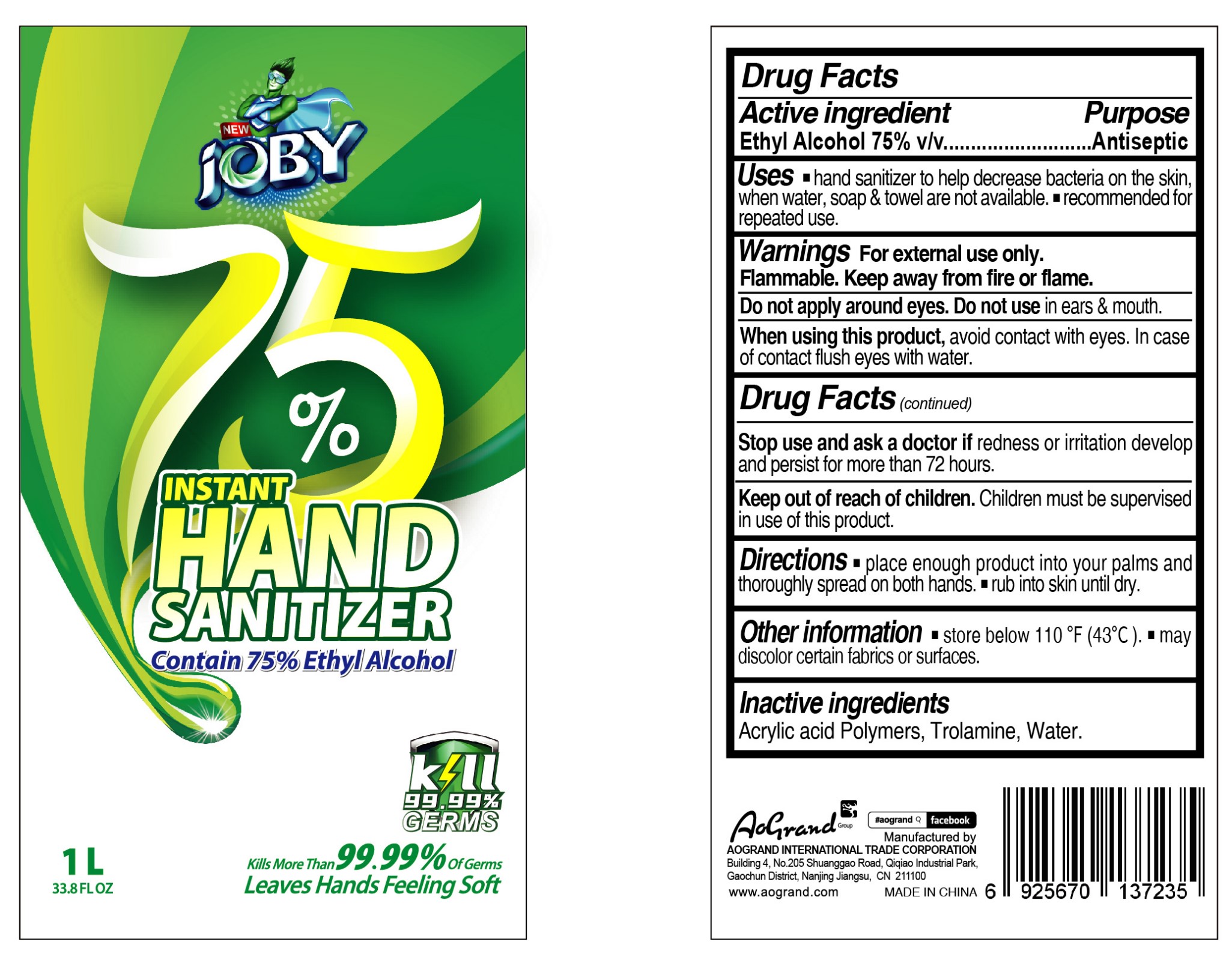 DRUG LABEL: Joby instant hand sanitrizer
NDC: 75617-003 | Form: GEL
Manufacturer: JASPERS GLOBAL MANUFACTURING INC
Category: otc | Type: HUMAN OTC DRUG LABEL
Date: 20230213

ACTIVE INGREDIENTS: ALCOHOL 75 mL/100 mL
INACTIVE INGREDIENTS: TROLAMINE; CARBOMER HOMOPOLYMER, UNSPECIFIED TYPE; WATER

Joby instant hand sanitrizer

Active Ingredient

Ethyl Alcohol 75% v/v.

Purpose

Antiseptic

Uses

- hand sanitizer to help decrease bacteria on the skin, when water, soap & towel are not available.
- recommended for repeated use.

Warnings

For external use only. Flammable. Keep away from heat or flame

DO NOT USE

Do not apply around eyes. Do not use in ears & mouth.

When using this product, avoid contact with eyes. In case of contact flush eyes with water.

Stop use and ask a doctor if redness or irritation develop and persist for more than 72 hours.

Keep out of reach of children. Children must be supervised in use of this product.

Directions

- place enough product into your palms and thoroughly spread on both hands.
- rub into skin until dry.

Inactive ingredients

carbomer, triethanolamine, water.

Other information

- store below 110 ℉ (43 ℃).
- may discolor certain fabrics or surfaces.

Package Label - Principal Display Panel

75617-003-01 500 mL

75617-003-02 1000 mL